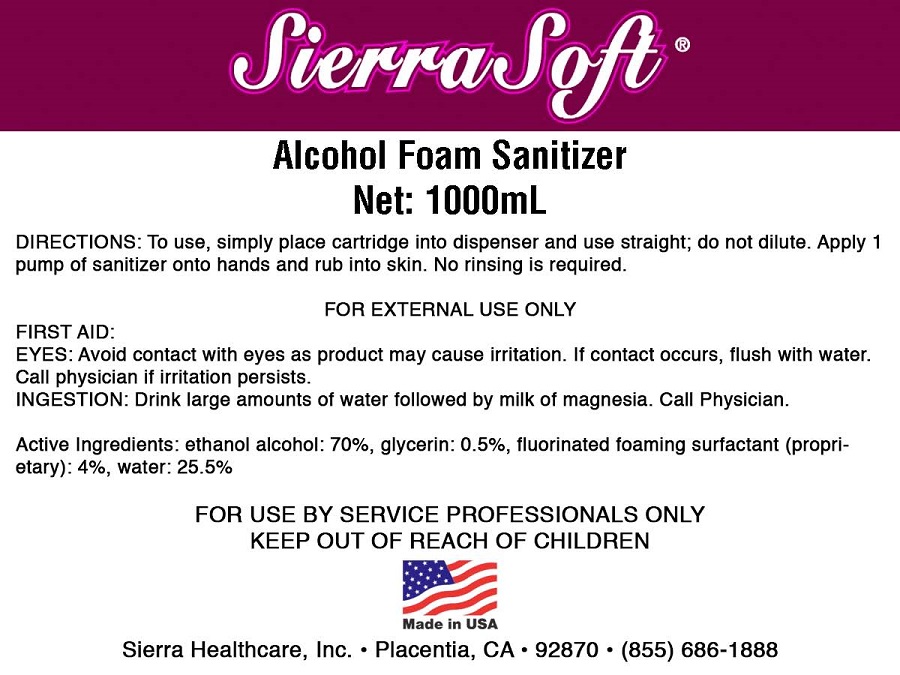 DRUG LABEL: Sierra Soft Alcohol Foam Sanitizer
NDC: 70415-102 | Form: GEL
Manufacturer: CWGC LA Inc.
Category: otc | Type: HUMAN OTC DRUG LABEL
Date: 20230921

ACTIVE INGREDIENTS: ALCOHOL 1 g/100 mL
INACTIVE INGREDIENTS: GLYCERIN; POLYTETRAFLUOROETHYLENE; ACETIC ACID; WATER

CWGC - SIERRA SOFT ALCOHOL FOAM SANITIZER (70415-102)

Active ingredient

Ethyl Alcohol 70%

Purpose

Antibacterial

Uses

- For sanitizing to reduce bacteria on the skin.

Warnings

For external use only

Keep out of reach of children. If swallowed, get medical help or contact a Poison Control Center right away.

Directions

TO USE, SIMPLY PLACE CARTRIDGE INTO DISPENSER AND USE STRAIGHT; DO NOT DILUTE. APPLY 1 PUMP OF SANITIZER ONTO HANDS AND RUB INTO SKIN. NO RINSING REQUIRED.

Inactive ingredients

GLYCERIN, FLUORINATED FOAMING SURFACTANT (PROPRIETARY), WATER.